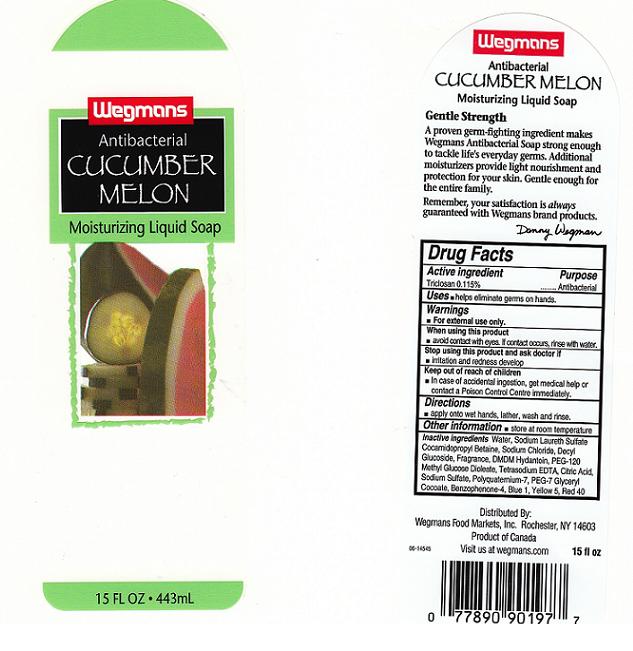 DRUG LABEL: Wegmans
NDC: 47124-232 | Form: SOAP
Manufacturer: Wegman Food Markets Inc
Category: otc | Type: HUMAN OTC DRUG LABEL
Date: 20101007

ACTIVE INGREDIENTS: TRICLOSAN 0.115 mL/100 mL
INACTIVE INGREDIENTS: WATER; SODIUM LAURETH SULFATE; COCAMIDOPROPYL BETAINE; SODIUM CHLORIDE; POLYQUATERNIUM-7 (70/30 ACRYLAMIDE/DADMAC; 1600 KD); DMDM HYDANTOIN; EDETATE SODIUM; CITRIC ACID MONOHYDRATE; PEG-120 METHYL GLUCOSE DIOLEATE; BENZOPHENONE; FD&C RED NO. 40; FD&C BLUE NO. 1; FD&C YELLOW NO. 5

Active Ingredient

Triclosan 0.115%

Purpose

Antibacterial

Warnings

For external use only.

When using this product

- Avoid contact with eyes. If contact occurs, rinse with water.

Stop using this product and ask doctor if

- irritation or redness develops and lasts.

Keep out of reach of children

In case of accidental ingestion, get medical help or contact a Poison Control Center immediately.

Directions

Apply onto wet hands, work into a lather, rinse thoroughly.

Uses

Helps reduce bacteria on the skin

Inactive Ingredients

Water, Sodium Laureth Sulfate, Cocamide MEA, Cocamidopropyl Betaine, Decyl Glucoside, Sodium Chloride, Fragrance (Parfum), DMDM Hydantoin, PEG-120 Methyl Glucose Dioleate, Citric Acid, Tetrasodium EDTA, Polyquaternium-7, PEG- 7 Glyceryl Cocoate, Benzophenone-4, Red 40, Blue 1, Yellow 5.

Package Front and Back Labels

weg.jpg